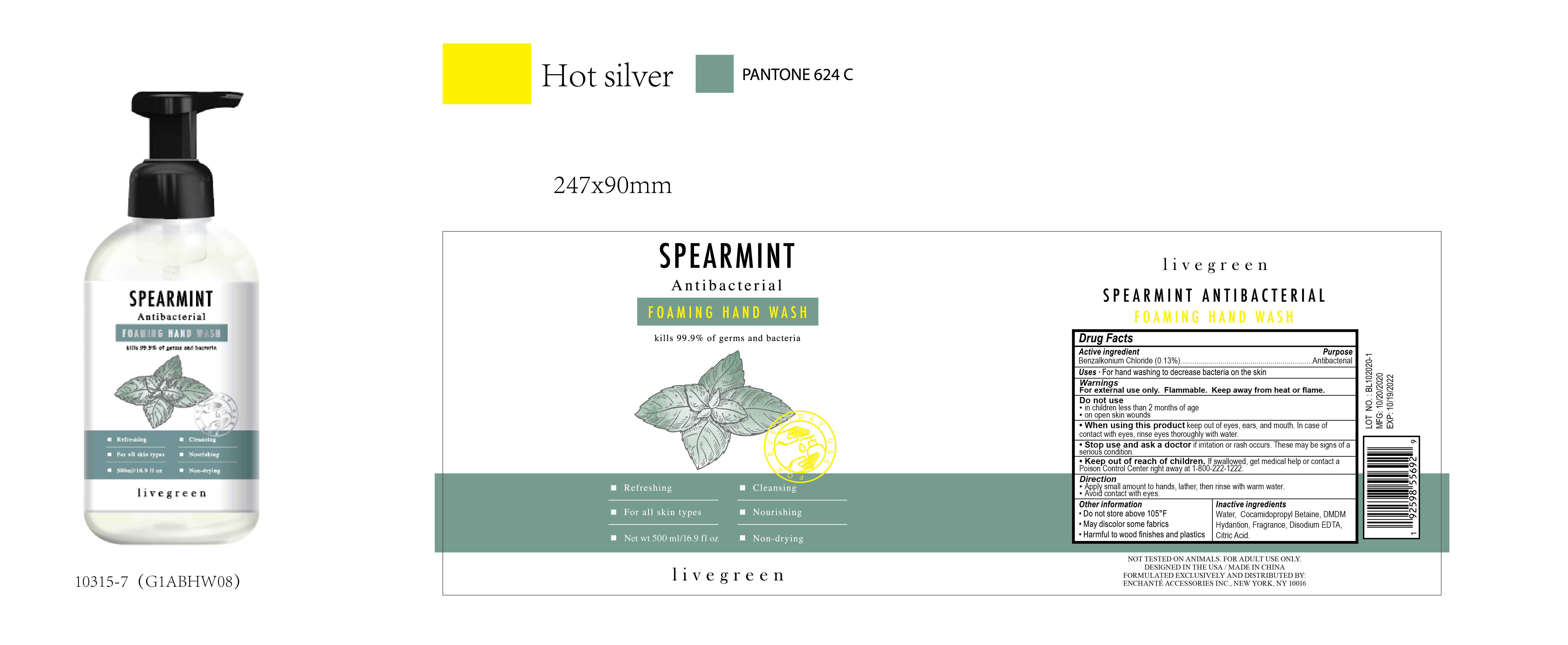 DRUG LABEL: livegreen SPEARMINT Antibacterial FOAMING HAND WASH
NDC: 50563-406 | Form: SOAP
Manufacturer: ENCHANTE ACCESSORIES INC.
Category: otc | Type: HUMAN OTC DRUG LABEL
Date: 20201101

ACTIVE INGREDIENTS: BENZALKONIUM CHLORIDE 0.13 g/100 mL
INACTIVE INGREDIENTS: COCAMIDOPROPYL BETAINE; DMDM HYDANTOIN; DISODIUM HEDTA; CITRIC ACID MONOHYDRATE; WATER

50563-406/G1ABHW08

Active Ingredient

Benzalkonium Chloride 0.13%

Purpose

Antibacterial

Use

■ For hand washing to decrease bacteria on the skin

WARNINGS

For external use only. Flammable. Keep away from heat or flame

Do not use

- in children less than 2 months of age
- on open skin wound

When using this product, keep out of eyes, ears, and mouth. In case of contact with eyes, rinse eyes thoroughly with water.

Stop use and ask a doctor if irritation or rash occurs. These may be signs of a serious condition

Keep out of reach of children. If swallowed, get medical help or contact a Poison Control Center right away at 1-800-222-1222

Directions

Apply a small amount to hands, lather, then rinse with warm water.

Avoid contact with eyes

Other Information

Do not store above 105F

May discolor some fabrics

Harmful to wood finishes and plastics

Inactive ingredients

Water, Cocamidopropyl Betaine, DMDM Hydantoin, Fragrance, Disodium EDTA, Citric Acid